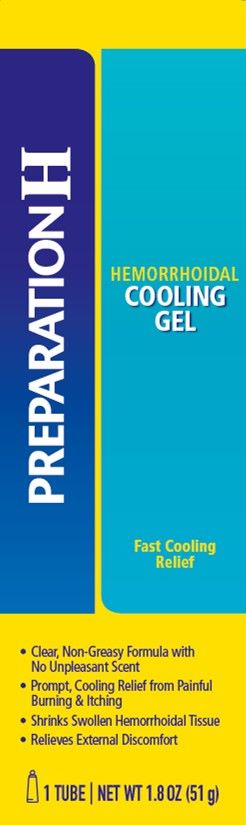 DRUG LABEL: Preparation H Cooling Gel
NDC: 0573-2840 | Form: GEL
Manufacturer: Haleon US Holdings LLC
Category: otc | Type: HUMAN OTC DRUG LABEL
Date: 20240405

ACTIVE INGREDIENTS: PHENYLEPHRINE HYDROCHLORIDE 2.5 mg/1 g; WITCH HAZEL 500 mg/1 g
INACTIVE INGREDIENTS: ALOE VERA LEAF; EDETATE DISODIUM; HYDROXYETHYL CELLULOSE (140 MPA.S AT 5%); METHYLPARABEN; POLYSORBATE 80; PROPYLENE GLYCOL; PROPYLPARABEN; WATER; SODIUM CITRATE, UNSPECIFIED FORM; SULISOBENZONE; .ALPHA.-TOCOPHEROL ACETATE

Drug Facts

Active ingredients

Phenylephrine HCl 0.25%

Witch hazel 50.0%

Purposes

Vasoconstrictor

Astringent

Uses

- helps relieve the local itching and discomfort associated with hemorrhoids
- temporary relief of irritation and burning
- temporarily shrinks hemorrhoidal tissue
- aids in protecting irritated anorectal areas

Warnings

For external use only

Ask a doctor before use if you have

- heart disease
- high blood pressure
- thyroid disease
- diabetes
- difficulty in urination due to enlargement of the prostate gland

Ask a doctor or pharmacist before use if you are

presently taking a prescription drug for high blood pressure or depression.

When using this product

- do not exceed the recommended daily dosage unless directed by a doctor
- do not put this product into the rectum by using fingers or any mechanical device or applicator

Stop use and ask a doctor if

- bleeding occurs
- condition worsens or does not improve within 7 days

If pregnant or breast-feeding,

ask a health professional before use.

Keep out of reach of children.

If swallowed, get medical help or contact a Poison Control Center right away.

Directions

- adults: when practical, cleanse the affected area by patting or blotting with an appropriate cleansing wipe. Gently dry by patting or blotting with a tissue or a soft cloth before applying gel.
- when first opening the tube, puncture foil seal with top end of cap
- apply externally to the affected area up to 4 times daily, especially at night, in the morning or after each bowel movement
- children under 12 years of age: ask a doctor

Other information

store at 20-25°C (68-77°F)

Inactive ingredients

aloe barbadensis leaf juice, edetate disodium, hydroxyethyl cellulose, methylparaben, polysorbate 80, propylene glycol, propylparaben, purified water, sodium citrate, sulisobenzone, vitamin E acetate

Questions or comments?

Call weekdays 9 AM to 5 PM EST at 1-800-99PrepHor 1-800-997-7374

Additional information

Do Not Use if tube seal under cap embossed with “H” is broken or missing.

Distributed by: GSK Consumer Healthcare, Warren, NJ 07059

For most recent product information, visit www.preparationh.com

Trademarks owned or licensed by GSK

©2021 GSK or licensor

Made In Canada

Do Not Use if tube seal under cap embossed with “H” is broken or missing.

PRINCIPAL DISPLAY PANEL

PREPARATION H

HEMORRHOIDAL
COOLING
GEL

Fast Cooling
Relief

- Clear, Non-Greasy Formula with
  No Unpleasant Scent
- Prompt, Cooling Relief from Painful
  Burning & Itching
- Shrinks Swollen Hemorrhoidal Tissue
- Relieves External Discomfort

1 TUBE | NET WT 1.8 OZ (51 g)

PAA162794 Front Carton